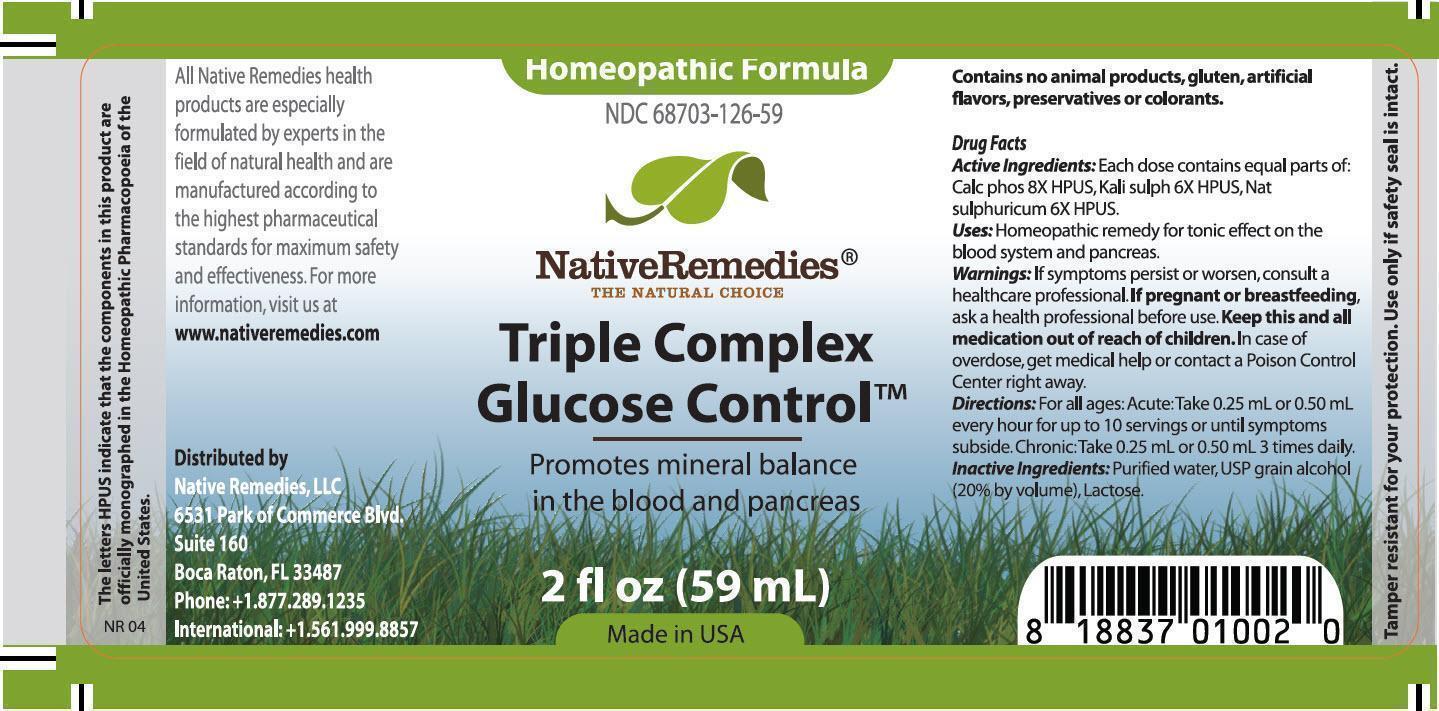 DRUG LABEL: Triple Complex Glucose Control
                
NDC: 68703-126 | Form: TINCTURE
Manufacturer: Native Remedies, LLC
Category: homeopathic | Type: HUMAN OTC DRUG LABEL
Date: 20140617

ACTIVE INGREDIENTS: TRIBASIC CALCIUM PHOSPHATE 8 [hp_X]/1 mL; POTASSIUM SULFATE 6 [hp_X]/1 mL; SODIUM SULFATE 6 [hp_X]/1 mL
INACTIVE INGREDIENTS: ALCOHOL; LACTOSE; WATER

Triple Complex Glucose Control

PURPOSE

Promotes mineral balance in the blood and pancreas

Drug Facts
Active Ingredients: Each dose contains equal parts of: Calc phos 8X HPUS, Kali sulph 6X HPUS, Nat sulphuricum 6X HPUS

INDICATIONS AND USAGE

Uses: Homeopathic remedy for tonic effect on the blood system and pancreas.

WARNINGS

Warnings: If symptoms persist or worsen, consult a healthcare professional

PREGNANCY OR BREAST FEEDING

If pregnant or breastfeeding, ask a health professional before use.

KEEP OUT OF REACH OF CHILDREN

Keep this and all medication out of reach of children

OVERDOSAGE

In case of overdose, get medical help or contact a Poison Control Center right away

DOSAGE AND ADMINISTRATION

Directions: For all ages: Acute: Take 0.25 mL or 0.50 mL every hour for up to 10 servings or until symptoms subside. Chronic: Take 0.25 mL or 0.50 mL 3 times daily

INACTIVE INGREDIENT

Inactive Ingredients: Purified water, USP grain alcohol (20% by volume), Lactose.

PATIENT COUNSELING INFORMATION

The letter HPUS indicate that the components in this product are officially monographed in the Homeopathic Pharmacopoeia of the United States.

All Native Remedies health products are especially formulated by experts in the field of natural health and are manufactured according to the highest pharmaceutical standards for maximum safety and effectiveness. For more information, visit us at www.nativeremedies.com

Distributed by
Native Remedies, LLC
6531 Park of Commerce Blvd.
Suite 160
Boca Raton, FL 33487
Phone: +1.877.289.1235
International:+1.561.999.8857

Contains no animal products, gluten, artificial flavors, preservatives or colorants.

STORAGE AND HANDLING

Tamper resistant for your protection. Use only if safety seal is intact.